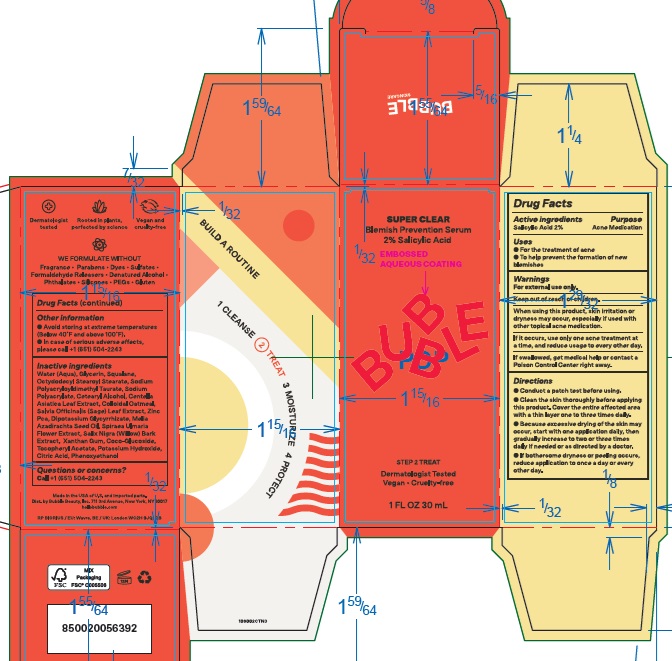 DRUG LABEL: Bubble Super Clear Blemish Prevention Serum
NDC: 83509-001 | Form: EMULSION
Manufacturer: BUBBLE BEAUTY
Category: otc | Type: HUMAN OTC DRUG LABEL
Date: 20240503

ACTIVE INGREDIENTS: SALICYLIC ACID 20 mg/1 mL
INACTIVE INGREDIENTS: OCTYLDODECYL STEAROYL STEARATE; OATMEAL; ZINC PIDOLATE; SALIX NIGRA BARK; POTASSIUM HYDROXIDE; ALPHA-TOCOPHEROL ACETATE; FILIPENDULA ULMARIA FLOWER; XANTHAN GUM; COCO-GLUCOSIDE; SAGE; AZADIRACHTA INDICA SEED OIL; CITRIC ACID MONOHYDRATE; SODIUM POLYACRYLOYLDIMETHYL TAURATE; WATER; PHENOXYETHANOL; GLYCERIN; SQUALANE; SODIUM POLYACRYLATE (2500000 MW); CENTELLA ASIATICA LEAF; CETOSTEARYL ALCOHOL; GLYCYRRHIZINATE DIPOTASSIUM

Bubble Super Clear Blemish Prevention Serum

Active ingredients

Salicylic Acid 2%

Purpose

Acne Medication

Uses

- For the treatment of acne
- To help prevent the formation of new blemishes

Warnings

For external use only.

Keep out of reach of children.

If swallowed, get medical help or contact a Poison Control Center right away.

When using this product

skin irritation or dryness may occur, especiallly if used with other topical acne medication. If it occurs, use only one acne treatment at a time, and reduce usage to every other day.

Directions

- Conduct a patch test before using.
- Clean the skin thoroughly before applying this product. Cover the entire affected area with a thin layer one to three times daily.
- Because excessive drying of the skin may occur, start with one application daily, then gradually increase to two or three times daily if needed or as directed by a doctor.
- If bothersome dryness or peeling occurs, reduce application to once a day or every other day.

Other information

- Avoid storing at extreme temperatures (Below 40F and above 100F).
- In case of serious adverse effects, please call +1 (651) 504-2243

Inactive ingredients

Water (Aqua), Glycerin, Squalane, Octyldodecyl Stearoyl Stearate, Sodium Polyacryloyldimethyl Taurate, Sodium Polyacrylate, Cetearyl Alcohol, Centella Asiatica Leaf Extract, Colloidal Oatmeal, Salvia Officinalis (Sage) Leaf Extract, Zinc Pca, Dipotassium Glycyrrhizate, Melia Azadirachta Seed Oil, Spiraea Ulmaria Flower Extract, Salix Nigra (Willow) Bark Extract, Xanthan Gum, Coco-Glucoside, Tocopheryl Acetate, Potassium Hydroxide, Citric Acid, Phenoxyethanol

Questions or concerns?

Call +1 (651) 504-2243